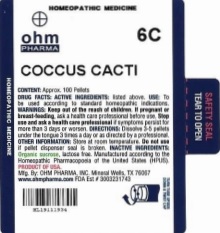 DRUG LABEL: Coccus Cacti
NDC: 66096-821 | Form: PELLET
Manufacturer: OHM PHARMA INC.
Category: homeopathic | Type: HUMAN OTC DRUG LABEL
Date: 20211230

ACTIVE INGREDIENTS: PROTORTONIA CACTI 6 [hp_C]/6 [hp_C]
INACTIVE INGREDIENTS: SUCROSE

COCCUS CACTI

DRUG FACTS: ACTIVE INGREDIENTS: COCCUS CACTI

CONTENT: Approx. 100 Pellets

INDICATIONS AND USAGE

USE: To be used according to standard homeopathic indications.

WARNINGS

WARNINGS: Keep out of reach of children. If pregnant or breast-feeding, ask a health care professional before use. Stop use and ask a health care professional if symptoms persist for more than 3 days or worsen.

Keep out of reach of children.

DOSAGE AND ADMINISTRATION

DIRECTIONS: Dissolve 3-5 pellets under the tongue 3 times a day or as directed by a professional.

OTHER INFORMATION: Store at room temperature. Do not use if pellet dispenser seal is broken.

INACTIVE INGREDIENTS: Organic sucrose, lactose free.

QUESTIONS

Manufactured according to the Homeopathic Pharmacopoeia of the United States (HPUS). PRODUCT OF USA.

Mfg. By: OHM PHARMA, INC. Mineral Wells, TX 76067

www.ohmpharma.com FDA Est # 3003231743

PACKAGE LABEL

COCCUS CACTI

The OTC Potency range from Coccus Cacti 6X-30X, 3C-30C, 200C, 1M.

Standard bottle sizes for dilution-form can range from 30mL to 60mL.

PURPOSE

To be used according to standard homeopathic indications.